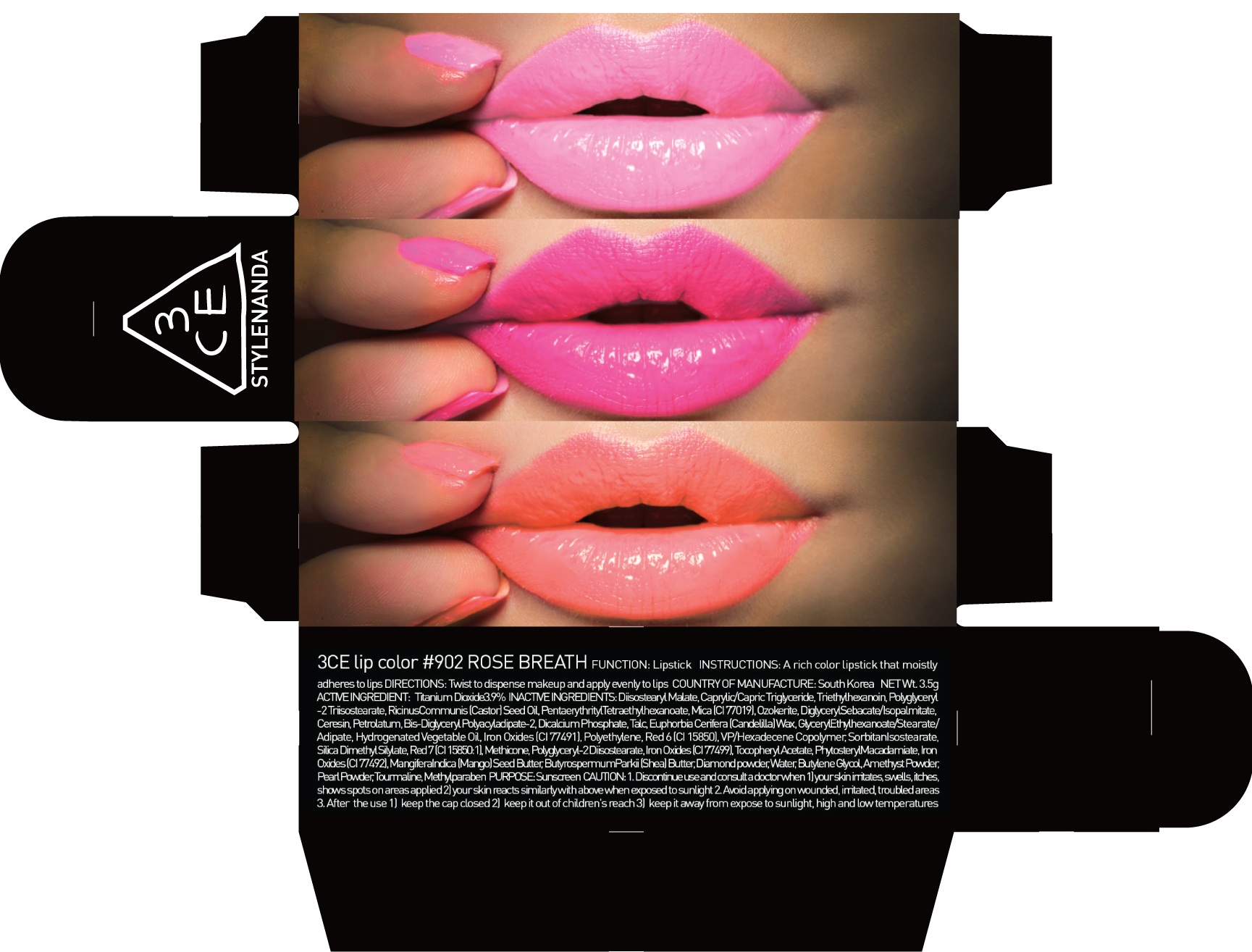 DRUG LABEL: 3CE LIP COLOR 902 ROSE BREATH
NDC: 60764-046 | Form: LIPSTICK
Manufacturer: Nanda Co., Ltd
Category: otc | Type: HUMAN OTC DRUG LABEL
Date: 20160930

ACTIVE INGREDIENTS: Titanium Dioxide 0.13 g/3.5 g
INACTIVE INGREDIENTS: Diisostearyl Malate; Triethylhexanoin

ACTIVE INGREDIENT

Active Ingredient: Titanium Dioxide 3.9%

INACTIVE INGREDIENT

Inactive Ingredients: Diisostearyl Malate, Caprylic/Capric Triglyceride, Triethylhexanoin, Polyglyceryl-2 Triisostearate, RicinusCommunis (Castor) Seed Oil, PentaerythritylTetraethylhexanoate, Mica (CI 77019), Ozokerite, DiglycerylSebacate/Isopalmitate, Ceresin, Petrolatum, Bis-Diglyceryl Polyacyladipate-2, Dicalcium Phosphate, Talc, Euphorbia Cerifera (Candelilla) Wax, GlycerylEthylhexanoate/Stearate/Adipate, Hydrogenated Vegetable Oil, Iron Oxides (CI 77491), Polyethylene, Red 6 (CI 15850), VP/Hexadecene Copolymer, SorbitanIsostearate, Silica Dimethyl Silylate, Red 7 (CI 15850:1), Methicone, Polyglyceryl-2 Diisostearate, Iron Oxides (CI 77499), Tocopheryl Acetate, PhytosterylMacadamiate, Iron Oxides (CI 77492), MangiferaIndica (Mango) Seed Butter, ButyrospermumParkii (Shea) Butter, Diamond powder, Water, Butylene Glycol, Amethyst Powder, Pearl Powder, Tourmaline, Methylparaben

PURPOSE

Purpose: Sunscreen

CAUTION

CAUTION: 1. Discontinue use and consult a doctor when - your skin irritates, swells, itches, shows spots on areas applied - your skin reacts similarly with above when exposed to sunlight 2. Avoid applying on wounded, irritated, troubled areas 3. After the use - keep the cap closed - keep it out of children's reach - keep it away from expose to sunlight, high and low temperatures

DESCRIPTION

INSTRUCTIONS: A rich color lipstick that moistly adheres to lips.

Directions: Twist to dispense makeup and apply evenly to lips